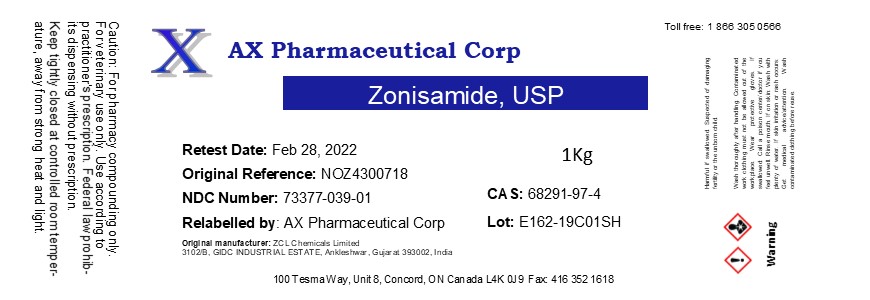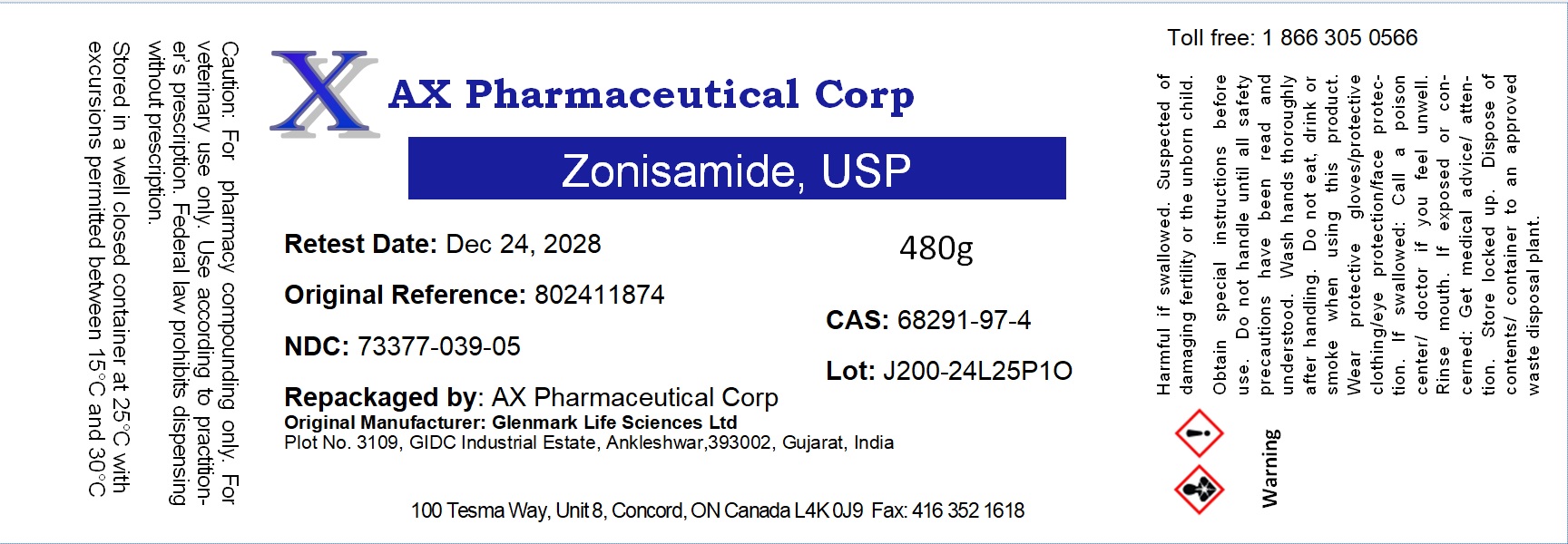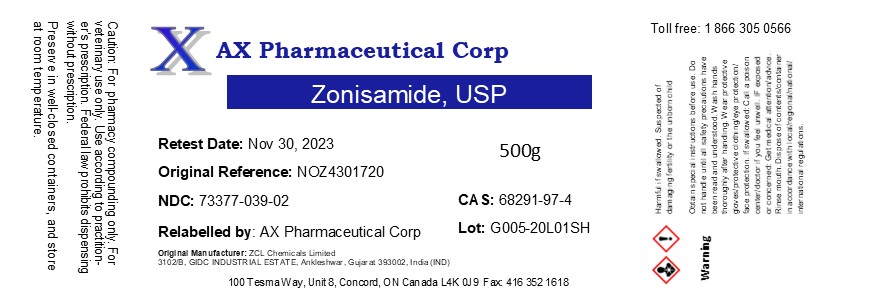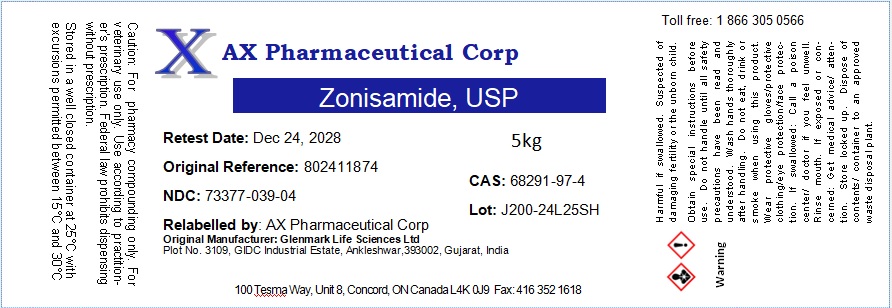 DRUG LABEL: Zonisamide
NDC: 73377-039 | Form: POWDER
Manufacturer: AX Pharmaceutical Corp
Category: other | Type: BULK INGREDIENT - ANIMAL DRUG
Date: 20250314

ACTIVE INGREDIENTS: ZONISAMIDE 1 kg/1 kg

Zonisamide